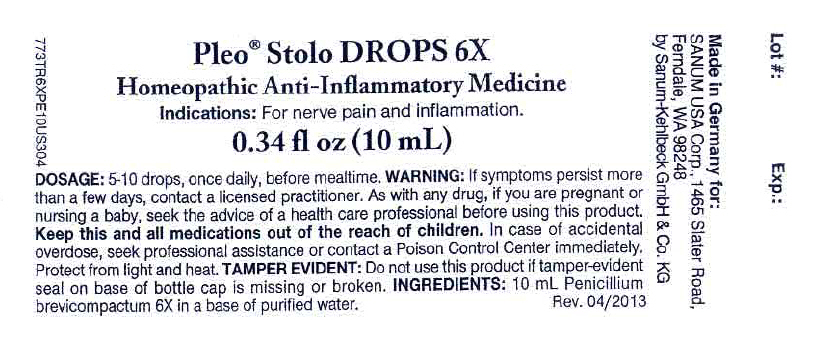 DRUG LABEL: Pleo Stolo
NDC: 60681-0011 | Form: SOLUTION/ DROPS
Manufacturer: Sanum Kehlbeck GmbH & Co. KG
Category: homeopathic | Type: HUMAN OTC DRUG LABEL
Date: 20130805

ACTIVE INGREDIENTS: penicillium brevicompactum 6 [hp_X]/10 mL
INACTIVE INGREDIENTS: water

Pleo® Stolo
DROPS 6X

Homeopathic Anti-Inflammatory Medicine

0.34 fl oz
(10 mL)

INDICATIONS AND USAGE

Indications

For nerve pain and inflammation.

INGREDIENTS

INACTIVE INGREDIENT

10 mL Penicillium brevicompactum 6X in a base of purified water.

Tamper Evident

Do not use this product if tamper-evident seal on base of bottle cap is missing or broken.

DOSAGE

5-10 drops, once daily, before mealtime.

WARNING

If symptoms persist more than a few days, contact a licensed practitioner. As with any drug, if you are pregnant or nursing a baby, seek the advice of a health care professional before using this product.

KEEP OUT OF REACH OF CHILDREN

Keep this and all other medications out of the reach of children. In case of accidental overdose, seek professional assistance or contact a Poison Control Center immediately.

STORAGE AND HANDLING

Protect fom light and heat.

Made in Germany

Distributed by:
SANUM USA Corp.
1465 Slater Road
Ferndale, WA 98248

Manufactured by:
Sanum-Kehlbeck
GmbH & Co. KG
Hoya, Germany

Rev. 03/2010

PRINCIPAL DISPLAY PANEL - 10 mL Bottle Label

Pleo® Stolo DROPS 6X
Homeopathic Anti-Inflammatory Medicine

Indications: For nerve pain and inflammation.

0.34 fl oz (10 mL)

DOSAGE: 5-10 drops, once daily, before mealtime. WARNING: If symptoms persist more
than a few days, contact a licensed practitioner. As with any drug, if you are pregnant or
nursing a baby, seek the advice of a health care professional before using this product.
Keep this and all medications out of the reach of children. In case of accidental
overdose, seek professional assistance or contact a Poison Control Center immediately.
Protect from light and heat. TAMPER EVIDENT: Do not use this product if tamper-evident
seal on base of bottle cap is missing or broken. INGREDIENTS: 10 mL Penicillium
brevicompactum 6X in a base of purified water.

Rev. 04/2013